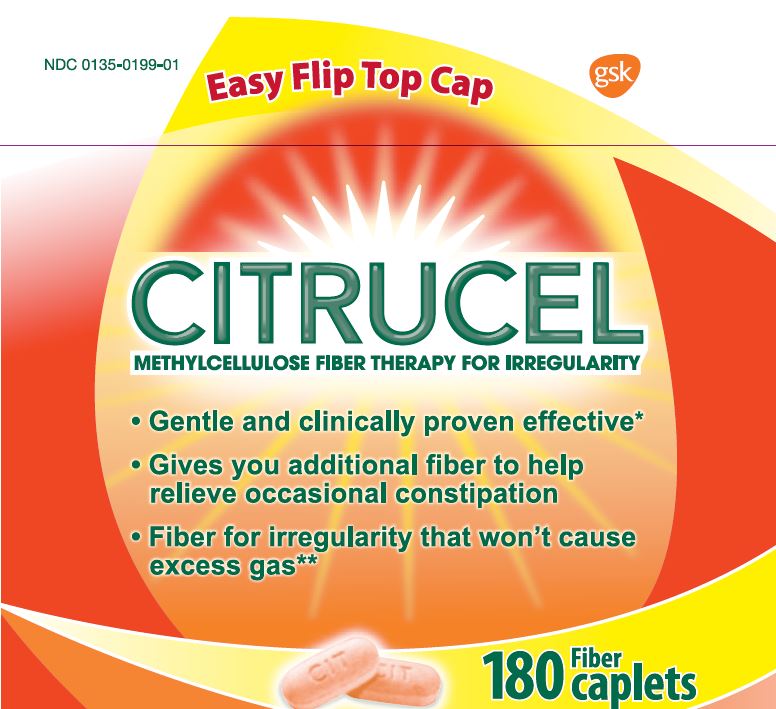 DRUG LABEL: CITRUCEL
NDC: 0135-0199 | Form: TABLET
Manufacturer: Haleon US Holdings LLC
Category: otc | Type: HUMAN OTC DRUG LABEL
Date: 20241205

ACTIVE INGREDIENTS: METHYLCELLULOSE (4000 MPA.S) 500 mg/1 1
INACTIVE INGREDIENTS: CROSPOVIDONE, UNSPECIFIED; ANHYDROUS DIBASIC CALCIUM PHOSPHATE; FD&C YELLOW NO. 6; MAGNESIUM STEARATE; MALTODEXTRIN; POVIDONE, UNSPECIFIED; SODIUM LAURYL SULFATE

Drug Facts

Active ingredient (in each caplet)

Methylcellulose (a non-allergenic fiber) 500mg

Purpose

Bulk-forming fiber laxative

Uses

- relieves occasional constipation (irregularity)
- generally produces a bowel movement in 12- 72 hours

Warnings

Choking: taking this product without adequate fluid may cause it to swell and block your throat or esophagus and may cause choking. Do not take this product if you have difficulty in swallowing. If you experience chest pain, vomiting, or difficulty in swallowing or breathing after taking this product, seek immediate medical attention.

Ask a doctor before use if you have

- a sudden change in bowel habits that persists for two weeks
- abdominal pain, nausea or vomiting

Stop use and ask a doctor if

- constipation lasts more than 7 days
- you have rectal bleeding

These could be signs of a serious condition.

Keep out of reach of children.

In case of overdose, get medical help or contact a Poison Control Center right away.

Directions

Take this product (child or adult dose) with at least 8 ounces (a full glass) of water or other fluid. Taking this product without enough liquid may cause choking. See choking warning.

Age | Dose | Maximum Dose
adults & children 12 years of age and over | start with 2 caplets. Increase as needed up to 6 times per day. | do not exceed 12 caplets per day
children 6 - 11 years of age | start with 1 caplet. Increase as needed up to 6 times per day. | do not exceed 6 caplets per day
children under 6 years of age | consult a physician | consult a physician

Other information

- each caplet contains: calcium 10mg
- store below 77 oF (25 oC)
- protect contents from humidity
- keep tightly closed

Inactive ingredients

crospovidone, dibasic calcium phosphate, FD&C yellow no. 6 aluminum lake, magnesium stearate, maltodextrin, povidone, sodium lauryl sulfate

Questions or comments?

call toll-free 1-800-897-6081

Additional information found on label

TAMPER EVIDENT PACKAGE

BOTTLE SEALED WITH PRINTED FOIL UNDER CAP.

DO NOT USE IF FOIL IS MISSING OR BROKEN.

Distributed by:

GSKConsumer Healthcare

Warren, NJ 07059

*When Used As Directed.

**Based On Laboratory Testing.

Individual Results May Vary.

Trademarks are owned by or licensed to the GSK group of companies

©2018 GSK or its licensor.

Principal Display Panel

NDC 0135-0199-01

CITRUCEL

METHYLCELLULOSE FIBER THERAPY FOR IRREGULARITY

Easy Flip Top Cap

- Gentle and clinically proven effective*
- Gives you additional fiber to help relieve occasional constipation
- Fiber for regularity that won’t cause excess gas**

180 Fiber caplets

105120XC